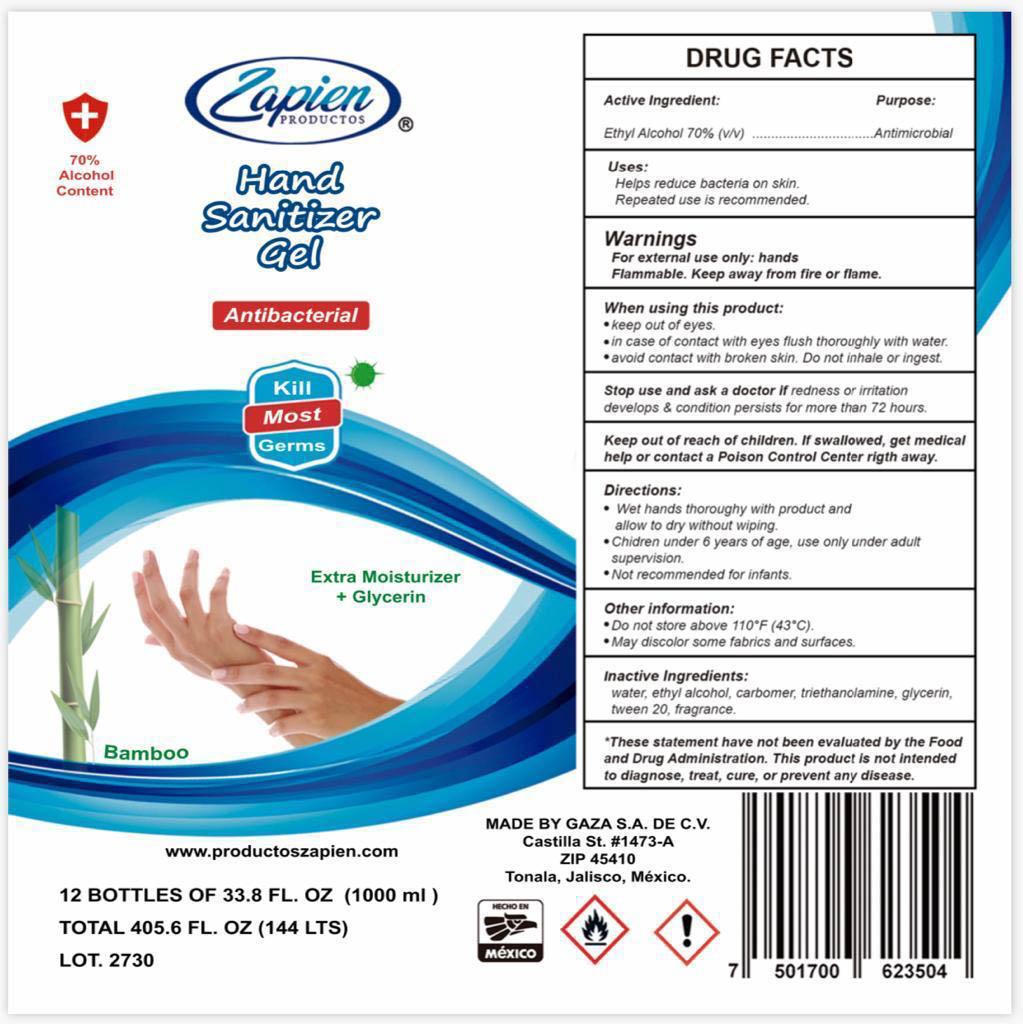 DRUG LABEL: Hand Sanitizer
NDC: 76938-100 | Form: GEL
Manufacturer: GAZA PROVEEDORA DE SERVICIOS DE HOSPEDAJE Y ALIMENTACION
Category: otc | Type: HUMAN OTC DRUG LABEL
Date: 20200428

ACTIVE INGREDIENTS: ALCOHOL 70 mL/100 mL
INACTIVE INGREDIENTS: GLYCERIN 10 mL/100 mL; CARBOMER 940 0.25 g/100 mL; WATER; THIOGLYCOLIC ACID TRIETHANOLAMINE 1.336 mL/100 mL; POLYSORBATE 20 3.33 g/100 mL

This is a rub hand sanitizer (leave in product) which is intended to be used when soap and water are not available, and are left on and not rinsed off with water. It complies with the final rule on consumer antiseptic rubs, using alcohol in a percentage between 65 and 90%. The product is made with

1. Alcohol (ethanol) (70%, volume/volume (v/v)) in an aqueous solution denatured.
2. Glycerol (10% v/v).
3. Isopropyl alcohol (1.33% v/v).
4. Sterile distilled water or boiled cold water.
5. Carbomer 940 (0.25% m/v)
6. Polysorbate 20 (3.33% m/v)

The firm add only fragrance (0.002%) as an inactive ingredient, and realizes it may impact the quality and potency of the product.

Active Ingredient(s)

Alcohol 70% v/v. Purpose: Antiseptic

Purpose

Antiseptic, Hand Sanitizer

Use

Hand Sanitizer to help reduce bacteria that potentially can cause disease. For use when soap and water are not available.

Warnings

For external use only. Flammable. Keep away from heat or flame

Do not use

- in children less than 2 months of age
- on open skin wounds

When using this product keep out of eyes, ears, and mouth. In case of contact with eyes, rinse eyes thoroughly with water.
Stop use and ask a doctor if irritation or rash occurs. These may be signs of a serious condition.
Keep out of reach of children. If swallowed, get medical help or contact a Poison Control Center right away.

Stop use and ask a doctor if irritation or rash occurs. These may be signs of a serious condition.

Keep out of reach of children. If swallowed, get medical help or contact a Poison Control Center right away.

Directions

- Place enough product on hands to cover all surfaces. Rub hands together until dry.
- Supervise children under 6 years of age when using this product to avoid swallowing.

Other information

- Store between 15-30C (59-86F)
- Avoid freezing and excessive heat above 40C (104F)

Inactive ingredients

glycerin, isopropyl alcohol, carbopol 940, polysorbate 20, fragrance, purified water USP

Package Label - Principal Display Panel

1000 mL NDC: 76540-100-01